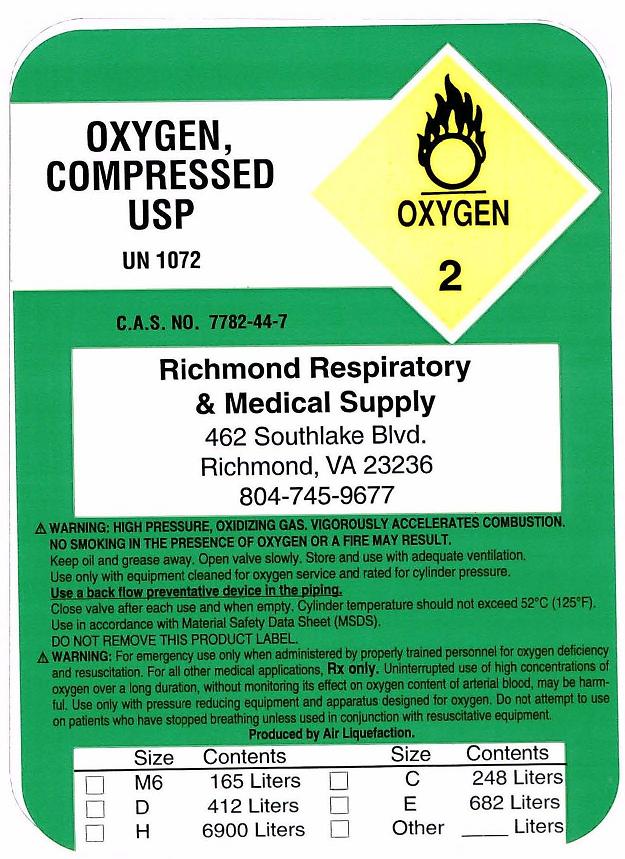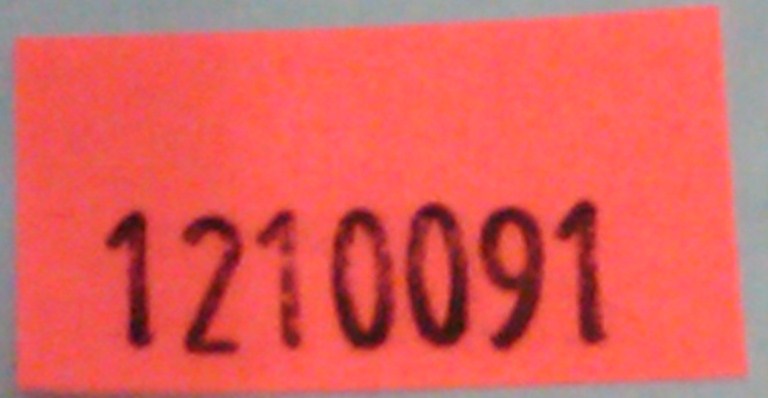 DRUG LABEL: Oxygen
NDC: 60561-0001 | Form: GAS
Manufacturer: Richmond Respiratory & Medical Supply
Category: prescription | Type: HUMAN PRESCRIPTION DRUG LABEL
Date: 20091218

ACTIVE INGREDIENTS: Oxygen 99 L/100 L

Oxygen